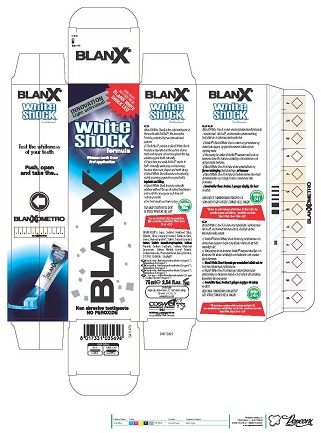 DRUG LABEL: BlanX White Shock
NDC: 70781-001 | Form: PASTE
Manufacturer: Coswell Spa
Category: otc | Type: HUMAN OTC DRUG LABEL
Date: 20200130

ACTIVE INGREDIENTS: SODIUM MONOFLUOROPHOSPHATE 0.82 g/100 g
INACTIVE INGREDIENTS: TITANIUM DIOXIDE; BENZYL ALCOHOL; PHENOXYETHANOL; SILICA DIMETHYL SILYLATE; ISOPROPYL ALCOHOL; SODIUM LAURYL SULFATE; SACCHARIN SODIUM; COPOVIDONE K25-31; SODIUM BENZOATE; FD&C BLUE NO. 1; CARBOXYMETHYLCELLULOSE SODIUM; GLYCERIN; CETRARIA ISLANDICA SUBSP. ISLANDICA; TRIBASIC CALCIUM PHOSPHATE; WATER; SORBITOL; HYDRATED SILICA

BlanX White Shock

ACTIVE INGREDIENT

SODIUM MONOFLUOROPHOSPHATE

INACTIVE INGREDIENTS

CETRARIA ISLANDICA EXTRACT

AQUA

HYDROXYPATITE

SORBITOL

HYDRATED SILICA

GLYCERIN

SILICA

ISOPROPYL ALCOHOL

SODIUM LAURYL SULFATE

CELLULOSE GUM

AROMA

CI 77891

SODIUM SACCHARIN

PVM/MA COPOLYMER

SODIUM BENZOATE

BENZYL ALCOHOL

PHENOXYETHANOL

CI 42090

PURPOSE

Naturally whitens and removes
bacteria that cause plaque and tooth decay

Keep out of reach of children

DOSAGE AND ADMINISTRATION

For best results use twice a day

INDICATIONS AND USAGE

For best results apply twice a day

WARNINGS

WARNING..DO NOT SWALLOW